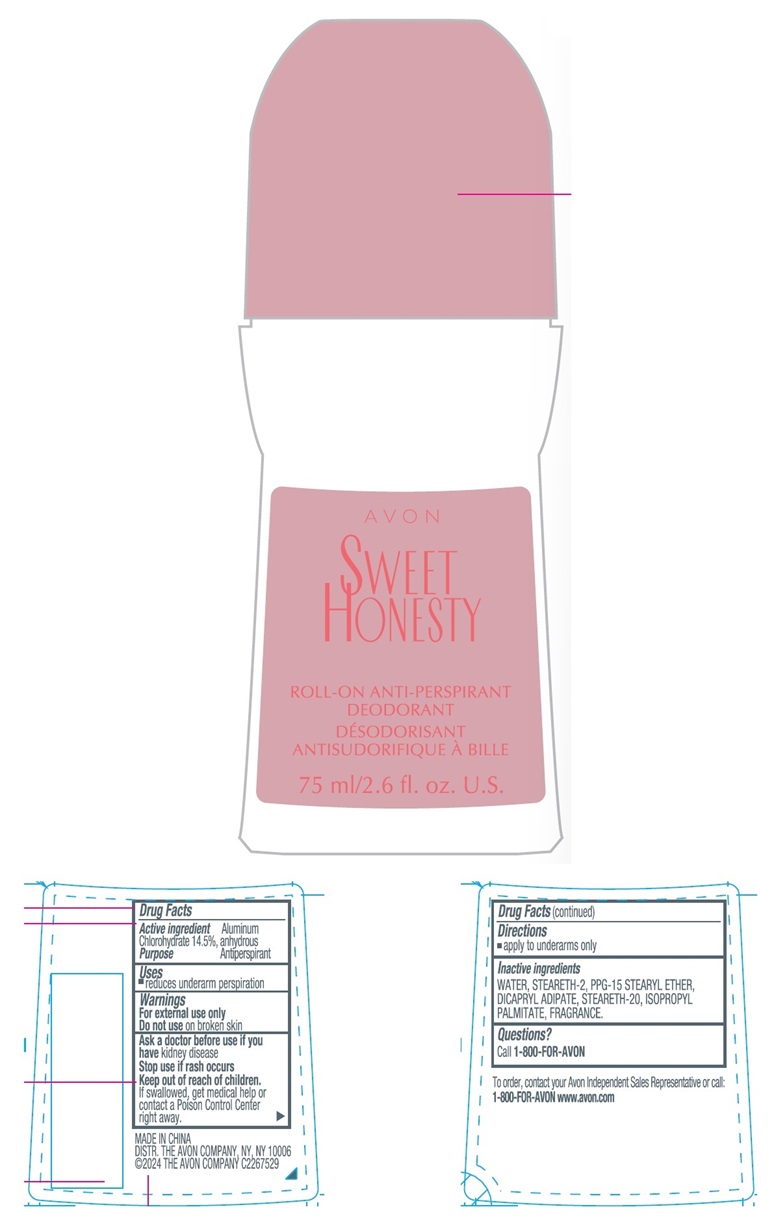 DRUG LABEL: AVON Sweet Honesty
NDC: 10096-1475 | Form: STICK
Manufacturer: The Avon Company
Category: otc | Type: HUMAN OTC DRUG LABEL
Date: 20240524

ACTIVE INGREDIENTS: ALUMINUM CHLOROHYDRATE 145 mg/1 mL
INACTIVE INGREDIENTS: STEARETH-2; WATER; DICAPRYL ADIPATE; PPG-15 STEARYL ETHER; STEARETH-20; ISOPROPYL PALMITATE

AVON Sweet Honesty Roll-On Anti-Perspirant Deodorant 75ml

Active ingredient

Aluminum Chlorohydrate 14.5% anhydrous

Purpose

Antiperspirant

Uses

- reduces underarm perspiration

Warnings

For external use only

Do not use on broken skin

Ask a doctor before use if you have kidney disease

Stop use if rash occurs

Keep out of reach of children.
If swallowed, get medical help or contact a Poison Control Center right away.

Directions

- apply to underarms only

Inactive ingredients

WATER, STEARETH-2, PPG-15 STEARYL ETHER, DICAPRYL ADIPATE, STEARETH-20, ISOPROPYL PALMITATE, FRANGRANCE

Questions?

Call 1-800-FOR-AVON

To order, contact your Avon Independent Sales Representative or call:
1-800-FOR-AVON www.avon.com

MADE IN CHINA
DIST. THE AVON COMPANY, NY, NY 10006
©2024 THE AVON COMPANY C2267529

Principal Display Panel

AVON
SWEET
HONESTY
ROLL-ON ANTI-PERSPIRANT
DEODORANT
75 ml/2.6 fl. oz. U.S.